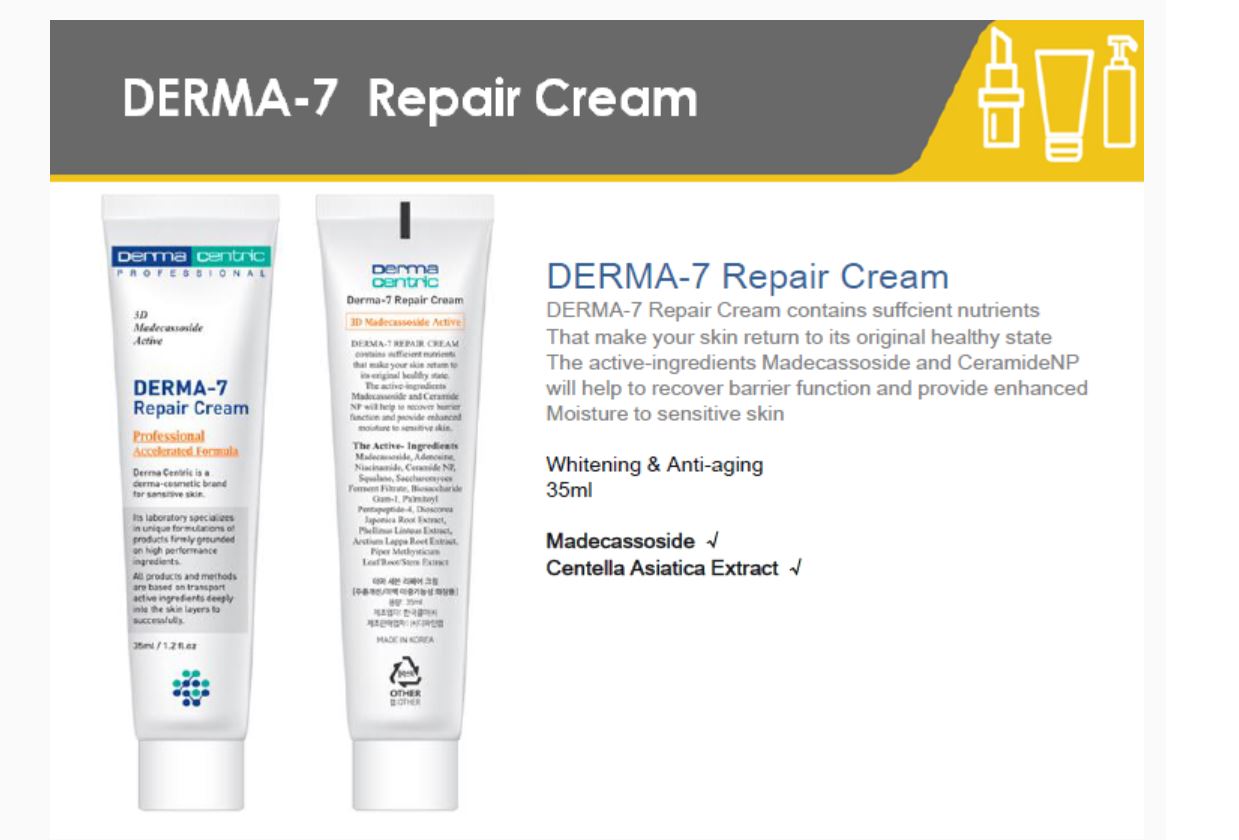 DRUG LABEL: DERMA 7 REPAIRCREAM
NDC: 79593-0002 | Form: CREAM
Manufacturer: DERMA CENTRIC INC
Category: otc | Type: HUMAN OTC DRUG LABEL
Date: 20200808

ACTIVE INGREDIENTS: NIACINAMIDE 2 g/100 mL; ADENOSINE 0.04 g/100 mL
INACTIVE INGREDIENTS: WATER; GLYCERIN

ACTIVE INGREDIENT

adenosine, niacinamide

PURPOSE

skin protectant

KEEP OUT OF REACH OF THE CHILDREN

WARNINGS

■ For external use only.

■ Do not use in eyes.

■ lf swallowed, get medical help promptly.

■ Stop use, ask doctor lf irritation occurs.

■ Keep out of reach of children.

DOSAGE AND ADMINISTRATION

for external use only

INACTIVE INGREDIENT

WATER
GLYCERIN
METHYLPROPANEDIOL
HYDROGENATED POLY(C6-14 OLEFIN)
CYCLOPENTASILOXANE
DIMETHICONE
NEOPENTYL GLYCOL DIHEPTANOATE
BETAINE
CAPRYLIC/CAPRIC TRIGLYCERIDE
1,2-HEXANEDIOL
POLYGLYCERYL-3 METHYLGLUCOSE DISTEARATE
DIOSCOREA JAPONICA ROOT EXTRACT
CETYL ALCOHOL
PHELLINUS LINTEUS EXTRACT
ARCTIUM LAPPA ROOT EXTRACT
PIPER METHYSTICUM LEAF/ROOT/STEM EXTRACT
HYDROGENATED LECITHIN
ARGANIA SPINOSA KERNEL OIL
SODIUM HYALURONATE
GLYCINE SOJA (SOYBEAN) OIL
SACCHAROMYCES FERMENT FILTRATE
PENTAERYTHRITYL DISTEARATE
POLYSORBATE 20
GLYCERYL STEARATE
PEG-100 STEARATE
POLYACRYLATE-13
POLYISOBUTENE
DIMETHICONE CROSSPOLYMER
SQUALANE
HYDROGENATED POLYISOBUTENE
ISONONYL ISONONANOATE
POLYGLYCERYL-10 STEARATE
MADECASSOSIDE
ALCOHOL
TOCOPHERYL ACETATE
POLYQUATERNIUM-51
GLYCOSYL TREHALOSE
ALCOHOL DENAT
LAURETH-4
CETEARYL ALCOHOL
CETYL ETHYLHEXANOATE
STEARIC ACID
ISOCETYL STEARATE
LAURETH-23
SODIUM STEAROYL GLUTAMATE
STEARYL HEPTANOATE
ALLANTOIN
HYDROGENATED STARCH HYDROLYSATE
RAFFINOSE
BIOSACCHARIDE GUM-1
BUTYROSPERMUM PARKII (SHEA) BUTTER
POLYGLYCERYL-2 DIPOLYHYDROXYSTEARATE
DISODIUM EDTA
LECITHIN
PEG-8 STEARATE
BUTYLENE GLYCOL
PANTHENOL
INULIN LAURYL CARBAMATE
FOLIC ACID
DISODIUM STEAROYL GLUTAMATE
CERAMIDE NP
CHOLESTEROL
TROMETHAMINE
PALMITOYL PENTAPEPTIDE-4
FRAGRANCE
ETHYLHEXYLGLYCERIN

INDICATIONS AND USAGE

apply proper amount to the skin